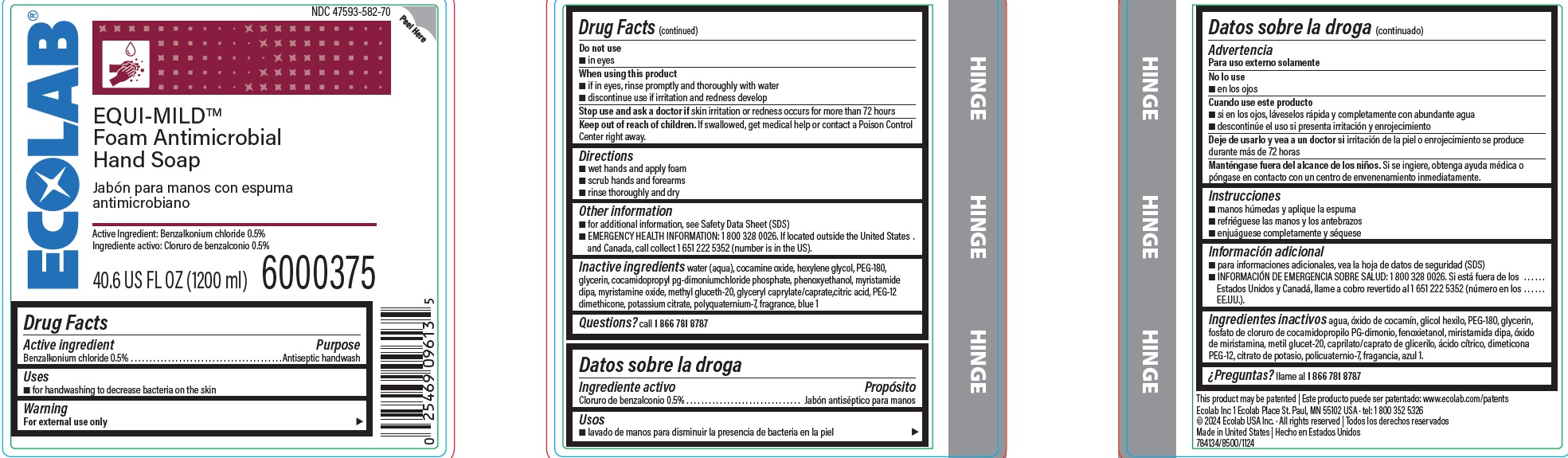 DRUG LABEL: Equi-Mild
NDC: 47593-582 | Form: SOLUTION
Manufacturer: Ecolab Inc.
Category: otc | Type: HUMAN OTC DRUG LABEL
Date: 20250718

ACTIVE INGREDIENTS: BENZALKONIUM CHLORIDE 5 mg/1 mL
INACTIVE INGREDIENTS: WATER; COCAMINE OXIDE; HEXYLENE GLYCOL; POLYETHYLENE GLYCOL 8000; GLYCERIN; COCAMIDOPROPYL PROPYLENE GLYCOL-DIMONIUM CHLORIDE PHOSPHATE; PHENOXYETHANOL; MYRISTAMIDE DIPA; POLYQUATERNIUM-7 (70/30 ACRYLAMIDE/DADMAC; 1600000 MW); MYRISTAMINE OXIDE; METHYL GLUCETH-20; GLYCERYL CAPRYLATE/CAPRATE; ANHYDROUS CITRIC ACID; PEG-12 DIMETHICONE; POTASSIUM CITRATE; BLUE 1

Drug Facts

Active Ingredient

Benzalkonium chloride 0.5%

Purpose

Antiseptic handwash

Uses

- for handwashing to decrease bacteria on the skin

Warning

For external use only

Do not use

- in eyes

When using the product

- if in eyes, rinse promptly and thoroughly with water
- discontinue use if irritation and redness develop

Stop use and ask a doctor if skin irritation or redness occurs for more than 72 hours

Keep out of reach of children. If swallowed, get medical help or contact a Poison Control Center right away.

Directions

- wet hands and apply foam
- scrub hands and forearms
- rinse thoroughly and dry

Other information

- for additional information, see Safety Data Sheet (SDS)
- EMERGENCY HELATH INFORMATION: 1 800 328 0026, If located outside the United States and Canada, call collect 1 651 222 5352 (number is in the US).

INACTIVE INGREDIENT

Inactive ingredients water (aqua), cocamine oxide, hexylene glycol, PEG-180, glycerin, cocamidopropyl pg-dimoniumchloride phosphate, phenoxyethanol, Myristamide dipa, myristamine oxide, methyl gluceth-20, glyceryl caprylate/caprate,citric acid, PEG-12 dimethicone, potassium citrate, polyquaternium-7, fragrance, blue 1

Questions? call 1 866 781 8787

Representative Label and Principal Display Panel

NDC 47593-582-70

ECOLAB

EQUI-MILD™

Foam Antimicrobial

Hand Soap

Active Ingredient: 0.5% Benzalkonium chloride

Net Contents

40.6 US FL OZ (1200 mL) 6000375

Ecolab Inc 1 Ecolab Place St. Paul MN 55102 USA

© 2024 Ecolab USA Inc. · All rights reserved

Made in United States

784134/8500/1124